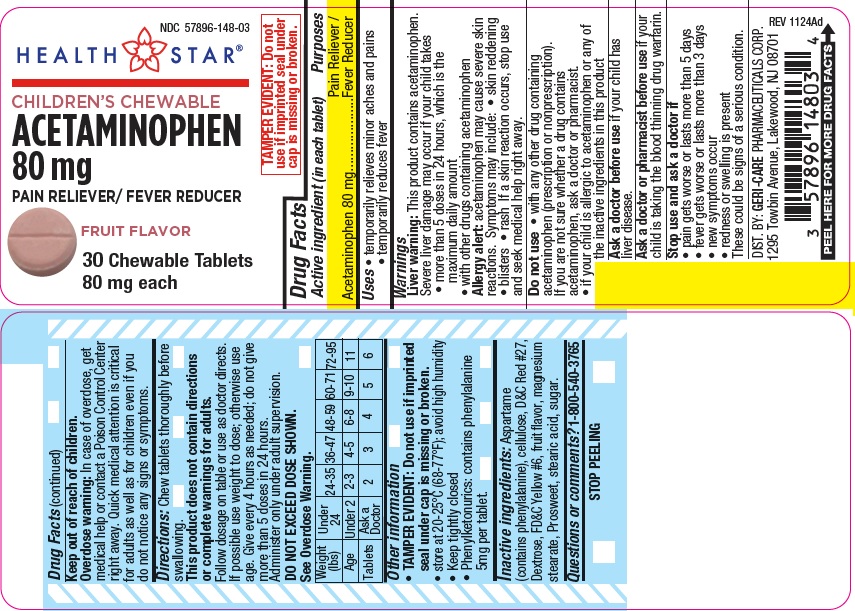 DRUG LABEL: Childrens Chewable Acetaminophen
NDC: 57896-148 | Form: TABLET, CHEWABLE
Manufacturer: GERI-CARE PHARMACEUTICAL CORP
Category: otc | Type: HUMAN OTC DRUG LABEL
Date: 20241128

ACTIVE INGREDIENTS: ACETAMINOPHEN 80 mg/1 1
INACTIVE INGREDIENTS: ASPARTAME; INVERT SUGAR; D&C RED NO. 27; DEXTROSE; FD&C YELLOW NO. 6; MAGNESIUM STEARATE; MICROCRYSTALLINE CELLULOSE; STEARIC ACID

hst148

Active ingredient (in each tablet)

Acetaminophen 80 mg

Purposes

Pain Reliever/Fever Reducer

Uses

- temporarily relieves minor aches and pains
- temporarily reduces fever

Warnings

Liver warning: This product contains acetaminophen. Severe liver damage may occur if your child takes:

- more than 5 doses in 24 hours, which is the maximum daily amount
- with other drugs containing acetaminophen

Allergy alert: Acetaminophen may cause severe skin reactions. Symptoms may include:

- skin reddening
- blisters
- rash

If a skin reaction occurs, stop use and seek medical help right away.

Do not use

- with any other drug containing acetaminophen (prescription or nonprescription). If you are not sure whether a drug contains acetaminophen, ask a doctor or pharmacist.
- if your child is allergic to acetaminophen or any of the inactive ingredients in this product

Ask a doctor before use if your child has

liver disease.

Ask a doctor or pharmacist before use if your child is

taking the blood thinning drug warfarin.

Stop use and ask a doctor if

- pain gets worse or lasts more than 5 days
- fever gets worse or lasts more than 3 days
- new symptoms occur
- redness or swelling is present

These could be signs of a serious condition.

Keep out of reach of children.

Overdose warning: In case of overdose, get medical
help or contact a Poison Control Center right away.
Quick medical attention is critical for adults as well as for
children even if you do not notice any signs or symptoms.

Directions

Chew tablets thoroughly before swallowing.
This product does not contain directions or complete
warnings for adults.
Follow dosage on table or use as doctor directs. If possible
use weight to dose; otherwise use age. Give every 4 hours
as needed; do not give more than 5 doses in 24 hours.
Administer only under adult supervision.
DO NOT EXCEED DOSE SHOWN

See Overdose Warning.

Weight (lb) | Under 24 | 24-35 | 36-47 | 48-59 | 60-71 | 72-95
Age | Under 2 | 2-3 | 4-5 | 6-8 | 9-10 | 11
Tablets | Ask a doctor | 2 | 3 | 4 | 5 | 6

Other information

- TAMPER EVIDENT: Do not use if imprinted seal under cap is missing or broken.
- store at 20°C-25°C (68°F-77°F)F); avoid high humidity
- Keep tightly closed
- Phenylketonurics: contains phenylalanine 5mg per tablet.

Inactive ingredients

Aspartame (contains phenylalanine), cellulose, D&C Red #27, Dextrose, FD&C Yellow #6, fruit flavor, magnesium stearate,
Prosweet, stearic acid, sugar

Questions or comments?

1-800-540-3765